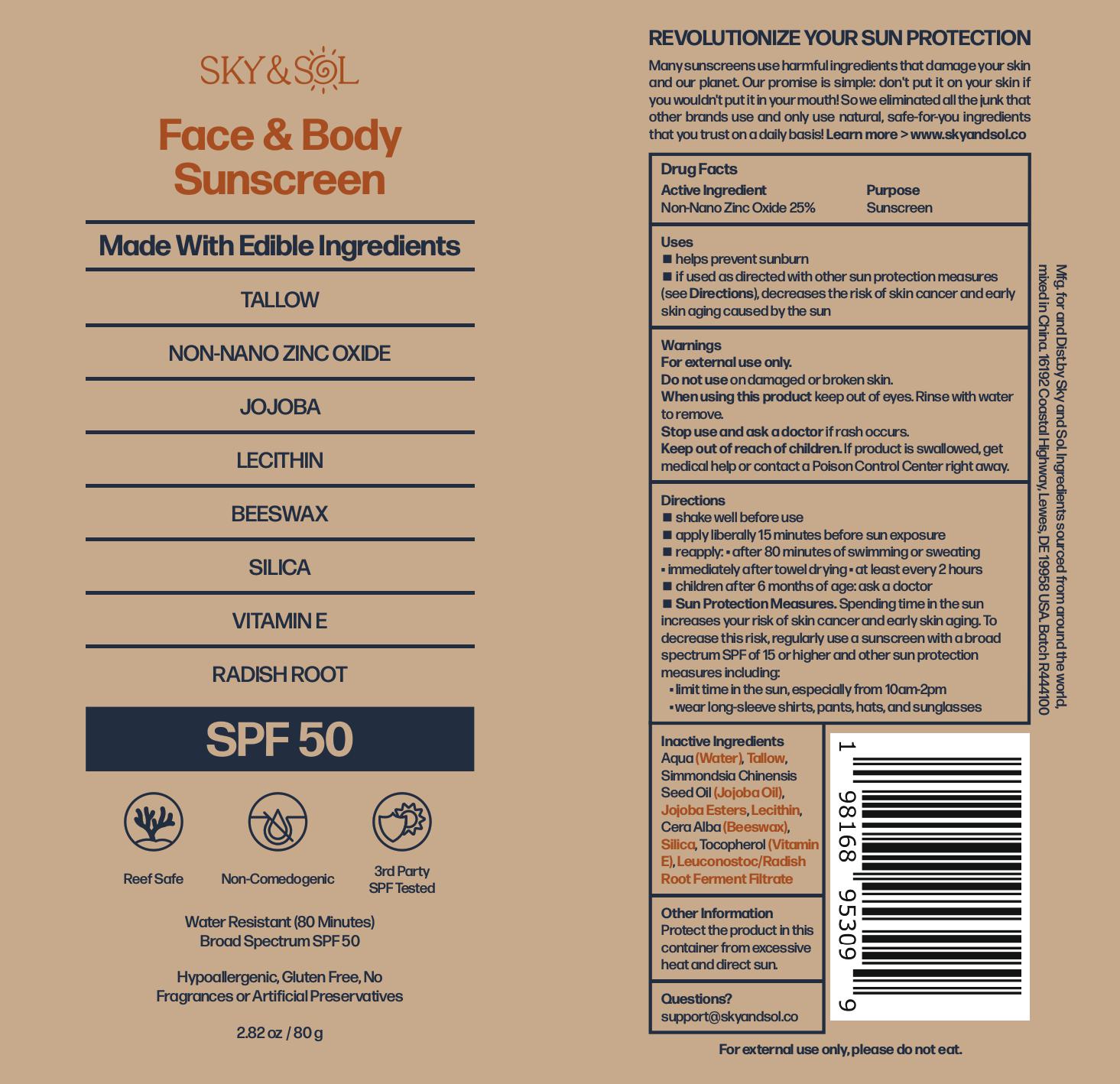 DRUG LABEL: Sky and Sol Sunscreen SPF 50
NDC: 84632-0503 | Form: CREAM
Manufacturer: Delta Ecommerce LLC
Category: otc | Type: HUMAN OTC DRUG LABEL
Date: 20250825

ACTIVE INGREDIENTS: ZINC OXIDE 25 g/100 g
INACTIVE INGREDIENTS: LIMONIA ACIDISSIMA BARK; JOJOBA OIL; LECITHIN, SUNFLOWER; BABASSU OIL; TALLOW; WATER; BEESWAX; LEUCONOSTOC/RADISH ROOT FERMENT FILTRATE

PURPOSE

Sunscreen

INDICATIONS AND USAGE

helps prevent sunburn; if used as directed with other sun protection measures (see Directions), decreases the risk of skin cancer and early skin aging caused by the sun.

DOSAGE AND ADMINISTRATION

Shake well before use.
Apply liberally 15 minutes before sun exposure.
Reapply:
after 80 minutes of swimming or sweating
immediately after towel drying
at least every 2 hours

INACTIVE INGREDIENT

Aqua (Water), Tallow, Simmondsia Chinensis (Jojoba) Seed Oil, Jojoba Esters, Lecithin, Cera Alba (Beeswax), Silica, Tocopherol (Vitamin E), Leuconostoc/Radish Root Ferment Filtrate

Warnings:
For external use only.
Do not use on damaged or broken skin.
Stop use and ask a doctor if rash occurs.
When using this product, keep out of eyes. Rinse with water to remove.

Keep out of reach of children. If swallowed, get medical help or contact a Poison Control Center right away.